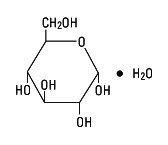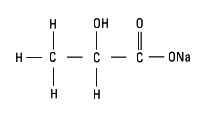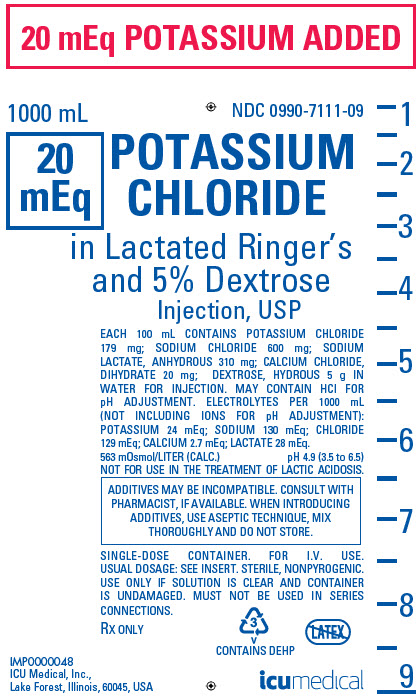 DRUG LABEL: Potassium Chloride in Lactated Ringers and Dextrose
NDC: 0990-7111 | Form: INJECTION, SOLUTION
Manufacturer: ICU Medical Inc.
Category: prescription | Type: HUMAN PRESCRIPTION DRUG LABEL
Date: 20251030

ACTIVE INGREDIENTS: POTASSIUM CHLORIDE 1.79 g/1000 mL; SODIUM CHLORIDE 6 g/1000 mL; CALCIUM CHLORIDE 0.2 g/1000 mL; SODIUM LACTATE 3.1 g/1000 mL; DEXTROSE MONOHYDRATE 50 g/1000 mL
INACTIVE INGREDIENTS: WATER

INTRAVENOUS SOLUTIONS WITH POTASSIUM CHLORIDE

POTASSIUM CHLORIDE IN LACTATED RINGER'S AND 5% DEXTROSE INJECTION, USP

Flexible Plastic Container

Rx only

DESCRIPTION

Intravenous solution with potassium chloride (I.V. solutions with KCl) is a sterile and nonpyrogenic solution in water for injection. This solution is for administration by intravenous infusion only.

See Table for summary of content and characteristics of this solution.

The solution contains no bacteriostat, antimicrobial agent or added buffer and is intended only for use as a single-dose injection. When smaller doses are required the unused portion should be discarded.

This solution is a parenteral fluid, nutrient and/or electrolyte replenisher.

Dextrose, USP is chemically designated D-glucose, monohydrate (C6H12O6 • H2O), a hexose sugar freely soluble in water. It has the following structural formula:

Potassium Chloride, USP is chemically designated KCl, a white granular powder freely soluble in water.

Sodium Chloride, USP is chemically designated NaCl, a white crystalline powder freely soluble in water.

Calcium Chloride, USP is chemically designated calcium chloride dihydrate (CaCl2 • 2H2O), white fragments or granules freely soluble in water.

Sodium Lactate, USP is chemically designated monosodium lactate [CH3CH(OH)COONa], a 60% aqueous solution miscible in water. It has the following structural formula:

Water for Injection, USP is chemically designated H20.

The flexible plastic container is fabricated from a specially formulated polyvinylchloride. Water can permeate from inside the container into the overwrap but not in amounts sufficient to affect the solution significantly. Solutions in contact with the plastic container may leach out certain chemical components from the plastic in very small amounts; however, biological testing was supportive of the safety of the plastic container materials. Exposure to temperatures above 25°C/77°F during transport and storage will lead to minor losses in moisture content. Higher temperatures lead to greater losses. It is unlikely that these minor losses will lead to clinically significant changes within the expiration period.

CLINICAL PHARMACOLOGY

When administered intravenously, this solution provides a source of water and electrolytes with carbohydrate calories.

Solutions containing carbohydrate in the form of dextrose restore blood glucose levels and provide calories. Carbohydrate in the form of dextrose may aid in minimizing liver glycogen depletion and exerts a protein-sparing action. Dextrose injected parenterally undergoes oxidation to carbon dioxide and water.

Calcium chloride in water dissociates to provide calcium (Ca^++) and chloride (Cl¯) ions. They are normal constituents of the body fluids and are dependent on various physiologic mechanisms for maintenance of balance between intake and output. Approximately 80% of body calcium is excreted in the feces as insoluble salts; urinary excretion accounts for the remaining 20%.

Sodium lactate provides sodium (Na^+) and lactate (C3H5O¯) ions. The lactate anion is in equilibrium with pyruvate and has an alkalizing effect resulting from simultaneous removal by the liver of lactate and hydrogen ions. In the liver, lactate is metabolized to glycogen which is ultimately converted to carbon dioxide and water by oxidative metabolism. The sodium (Na^+) ion combines with bicarbonate ion produced from carbon dioxide of the body and thus retains bicarbonate to combat metabolic acidosis (bicarbonate deficiency). The normal plasma level of lactate ranges from 0.9 to 1.9 mEqK/liter.

Intravenous solutions containing potassium chloride are particularly intended to provide needed potassium cation (K^+). Potassium is the chief cation of body cells (160 mEq/liter of intracellular water). It is found in low concentration in plasma and extracellular fluids (3.5 to 5.0 mEq/liter in a healthy adult). Potassium plays an important role in electrolyte balance. Normally about 80 to 90% of the potassium intake is excreted in the urine; the remainder in the stools and to a small extent, in the perspiration. The kidney does not conserve potassium well so that during fasting or in patients on a potassium-free diet, potassium loss from the body continues resulting in potassium depletion. A deficiency of either potassium or chloride will lead to a deficit of the other.

Sodium chloride in water dissociates to provide sodium (Na^+) and chloride (Cl¯) ions. Sodium (Na^+) is the principal cation of the extracellular fluid and plays a large part in the therapy of fluid and electrolyte disturbances. Chloride (Cl¯) has an integral role in buffering action when oxygen and carbon dioxide exchange occurs in the red blood cells. The distribution and excretion of sodium (Na^+) and chloride (Cl¯) are largely under the control of the kidney which maintains a balance between intake and output.

Water is an essential constituent of all body tissues and accounts for approximately 70% of total body weight. Average normal adult daily requirement ranges from two to three liters (1.0 to 1.5 liters each for insensible water loss by perspiration and urine production).

Water balance is maintained by various regulatory mechanisms. Water distribution depends primarily on the concentration of electrolytes in the body compartments and sodium (Na^+) plays a major role in maintaining physiologic equilibrium.

INDICATIONS AND USAGE

This solution is indicated in patients requiring parenteral administration of potassium chloride and the replacement of extracellular losses of fluids and electrolytes with minimal carbohydrate calories.

CONTRAINDICATIONS

Solutions containing potassium chloride are contraindicated in diseases where high potassium levels may be encountered.

Solutions containing lactate are NOT FOR USE IN THE TREATMENT OF LACTIC ACIDOSIS.

WARNINGS

Solutions containing calcium ions should not be administered simultaneously through the same administration set as blood because of the likelihood of coagulation.

Solutions which contain potassium ions should be used with great care, if at all, in patients with hyperkalemia, severe renal failure and in conditions in which potassium retention is present.

To avoid potassium intoxication, do not infuse these solutions rapidly. In patients with severe renal insufficiency or adrenal insufficiency, administration of potassium chloride may cause potassium intoxication.

Solutions containing sodium ions should be used with great care, if at all, in patients with congestive heart failure, severe renal insufficiency and in clinical states in which there exists edema with sodium retention.

In patients with diminished renal function, administration of solutions containing sodium or potassium ions may result in sodium or potassium retention.

Solutions containing lactate ions should be used with great care in patients with metabolic or respiratory alkalosis. The administration of lactate ions should be done with great care where there is an increased level or an impaired utilization of lactate ions, as in severe hepatic insufficiency.

The intravenous administration of this solution can cause fluid and/or solute overloading resulting in dilution of serum electrolyte concentrations, overhydration, congested states or pulmonary edema.

The risk of dilutional states is inversely proportional to the electrolyte concentration of administered parenteral solutions. The risk of solute overload causing congested states with peripheral and pulmonary edema is directly proportional to the electrolyte concentrations of such solutions.

PRECAUTIONS

Clinical evaluation and periodic laboratory determinations are necessary to monitor changes in fluid balance, electrolyte concentrations and acid-base balance during prolonged parenteral therapy or whenever the condition of the patient warrants such evaluation.

Solutions containing dextrose should be used with caution in patients with known subclinical or overt diabetes mellitus.

Caution must be exercised in the administration of parenteral fluids, especially those containing sodium ions, to patients receiving corticosteroids or corticotropin.

Potassium replacement therapy should be guided primarily by serial electrocardiograms. Plasma potassium levels are not necessarily indicative of tissue potassium levels.

High plasma concentrations of potassium may cause death through cardiac depression, arrhythmias or arrest.

Potassium-containing solutions should be used with caution in the presence of cardiac disease, particularly in digitalized patients or in the presence of renal disease.

Solutions containing lactate ions should be used with caution as excess administration may result in metabolic alkalosis.

Care should be exercised to insure that the needle (or catheter) is well within the lumen of the vein and that extravasation does not occur.

Do not administer unless solution is clear and container is undamaged. Discard unused portion.

Pregnancy Category C. Animal reproduction studies have not been conducted with dextrose, potassium chloride or Lactated Ringer’s Injection. It is also not known whether dextrose, potassium chloride or Lactated Ringer’s Injection can cause fetal harm when administered to a pregnant woman or can affect reproduction capacity. Dextrose, potassium chloride or Lactated Ringer’s Injection should be given to a pregnant woman only if clearly needed.

Pediatric Use:

The safety and effectiveness in the pediatric population are based on the similarity of the clinical conditions of the pediatric and adult populations. In neonates or very small infants the volume of fluid may affect fluid and electrolyte balance.

Frequent monitoring of serum glucose concentrations is required when dextrose is prescribed to pediatric patients, particularly neonates and low birth weight infants.

In very low birth weight infants, excessive or rapid administration of dextrose injection may result in increased serum osmolality and possible intracerebral hemorrhage.

ADVERSE REACTIONS

Reactions which may occur because of the solutions or technique of administration include febrile response, infection at the site of injection, venous thrombosis or phlebitis extending from the site of injection, extravasation and hypervolemia.

If an adverse reaction does occur, discontinue the infusion, evaluate the patient, institute appropriate therapeutic countermeasures and save the remainder of the fluid for examination if deemed necessary.

Nausea, vomiting, abdominal pain and diarrhea have been reported with potassium therapy. The signs and symptoms of potassium intoxication include paresthesias of the extremities, flaccid paralysis, listlessness, mental confusion, weakness and heaviness of the legs, hypotension, cardiac arrhythmias, heart block, electrocardiographic abnormalities such as disappearance of P waves, spreading and slurring of the QRS complex with development of a biphasic curve and cardiac arrest.

Potassium-containing solutions are intrinsically irritating to tissues. Therefore, extreme care should be taken to avoid perivascular infiltration. Local tissue necrosis and subsequent sloughing may result if extravasation occurs. Chemical phlebitis and venospasm have also been reported.

Should perivascular infiltration occur, I.V. administration at that site should be discontinued at once. Local infiltration of the affected area with procaine hydrochloride, 1%, to which hyaluronidase may be added, will often reduce venospasm and dilute the potassium remaining in the tissues locally. Local application of heat may also be helpful.

OVERDOSAGE

In the event of potassium overdosage, discontinue the infusion immediately and institute intensive corrective therapy to reduce serum potassium levels. (See WARNINGS and PRECAUTIONS.)

DOSAGE AND ADMINISTRATION

This solution should be administered only by intravenous infusion and as directed by the physician. The dose and rate of injection are dependent upon the age, weight and clinical condition of the patient. If the serum potassium level is greater than 2.5 mEq/liter, potassium should be given at a rate not to exceed 10 mEq/hour in a concentration less than 30 mEq/liter. Somewhat faster rates and greater concentrations (usually up to 40 mEq/liter) of potassium may be indicated in patients with more severe potassium deficiency. The total 24-hour dose should not generally exceed 200 mEq of potassium.

As reported in the literature, the dosage and constant infusion rate of intravenous dextrose must be selected with caution in pediatric patients, particularly neonates and low birth weight infants, because of the increased risk of hyperglycemia/hypoglycemia.

Drug Interactions

Additives may be incompatible. Consult with pharmacist, if available. When introducing additives, use aseptic technique, mix thoroughly and do not store.

The presence of calcium limits their compatibility with certain drugs that form precipitates of calcium salts, and also prohibits their simultaneous infusion through the same administration set as blood because of the likelihood of coagulation.

Parenteral drug products should be inspected visually for particulate matter and discoloration prior to administration, whenever solution and container permit. (See PRECAUTIONS.)

INSTRUCTIONS FOR USE

To Open

Tear outer wrap at notch and remove solution container. If supplemental medication is desired, follow directions below before preparing for administration. Some opacity of the plastic due to moisture absorption during the sterilization process may be observed. This is normal and does not affect the solution quality or safety. The opacity will diminish gradually.

To Add Medication

1. Prepare additive port.
2. Using aseptic technique and an additive delivery needle of appropriate length, puncture resealable additive port at target area, inner diaphragm and inject. Withdraw needle after injecting medication.
3. The additive port may be protected by covering with an additive cap.
4. Mix container contents thoroughly.

Preparation for Administration

(Use aseptic technique)

1. Close flow control clamp of administration set.
2. Remove cover from outlet port at bottom of container.
3. Insert piercing pin of administration set into port with a twisting motion until the set is firmly seated. NOTE: See full directions on administration set carton.
4. Suspend container from hanger.
5. Squeeze and release drip chamber to establish proper fluid level in chamber.
6. Open flow control clamp and clear air from set. Close clamp.
7. Attach set to venipuncture device. If device is not indwelling, prime and make venipuncture.
8. Regulate rate of administration with flow control clamp.

WARNING: Do not use flexible container in series connections.

HOW SUPPLIED

Intravenous solution with potassium chloride (I.V. solution with KCl) is supplied in single-dose flexible plastic container. See Table:

Potassium Chloride

in Lactated Ringer’s

and 5% Dextrose

Injection, USP

List No. | mEq; Potassium; Added | Size; (mL) | COMPOSITION (g/L) |  |  |  |  | Calculated; Osmolarity; (mOsmol/L)
List No. | mEq; Potassium; Added | Size; (mL) | Dextrose,; Hydrous | Potassium; Chloride | Sodium; Chloride | Sodium; Lactate,; Anhydrous | Calcium; Chloride; Dihydrate | Calculated; Osmolarity; (mOsmol/L)
7111 | 20 mEq | 1000 | 50 | 1.79 | 6 | 3.1 | 0.2 | 563
NDC No.
0409-7111-09
0990-7111-09

Potassium Chloride

in Lactated Ringer’s

and 5% Dextrose

Injection, USP (Continued)

pH | Approx. Ionic Concentrations (mEq/L) |  |  |  |  | Approx.; kcal/L
pH | Calcium; (Ca++) | Sodium; (Na^+) | Potassium; (K^+) | Chloride; (Cl¯) | Lactate | Approx.; kcal/L
4.9; (3.5 to 6.5) | 2.7 | 130 | 24 | 129 | 28 | 179

ICU Medical is transitioning NDC codes from the "0409" to a "0990" labeler code. Both NDC codes are expected to be in the market for a period of time.

May contain HCl for pH adjustment.

Store at 20 to 25°C (68 to 77°F). [See USP Controlled Room Temperature.] Protect from freezing.

Revised: March, 2020

IFU0000167

ICU Medical, Inc., Lake Forest, Illinois, 60045, USA

PRINCIPAL DISPLAY PANEL - 1000 mL Bag Label

20 mEq POTASSIUM ADDED

1000 mL
NDC 0990-7111-09

20
mEq
POTASSIUM
CHLORIDE

in Lactated Ringer's
and 5% Dextrose
Injection, USP

EACH 100 mL CONTAINS POTASSIUM CHLORIDE
179 mg; SODIUM CHLORIDE 600 mg; SODIUM
LACTATE, ANHYDROUS 310 mg; CALCIUM CHLORIDE,
DIHYDRATE 20 mg; DEXTROSE, HYDROUS 5 g IN
WATER FOR INJECTION. MAY CONTAIN HCl FOR
pH ADJUSTMENT. ELECTROLYTES PER 1000 mL
(NOT INCLUDING IONS FOR pH ADJUSTMENT):
POTASSIUM 24 mEq; SODIUM 130 mEq; CHLORIDE
129 mEq; CALCIUM 2.7 mEq; LACTATE 28 mEq.
563 mOsmol/LITER (CALC.)
pH 4.9 (3.5 to 6.5)
NOT FOR USE IN THE TREATMENT OF LACTIC ACIDOSIS.

ADDITIVES MAY BE INCOMPATIBLE. CONSULT WITH
PHARMACIST, IF AVAILABLE. WHEN INTRODUCING
ADDITIVES, USE ASEPTIC TECHNIQUE, MIX
THOROUGHLY AND DO NOT STORE.

SINGLE-DOSE CONTAINER. FOR I.V. USE.
USUAL DOSAGE: SEE INSERT. STERILE, NONPYROGENIC.
USE ONLY IF SOLUTION IS CLEAR AND CONTAINER
IS UNDAMAGED. MUST NOT BE USED IN SERIES
CONNECTIONS.

Rx ONLY
3
V
CONTAINS DEHP

IMP0000048

ICU Medical, Inc.,
Lake Forest, Illinois, 60045, USA
icumedical